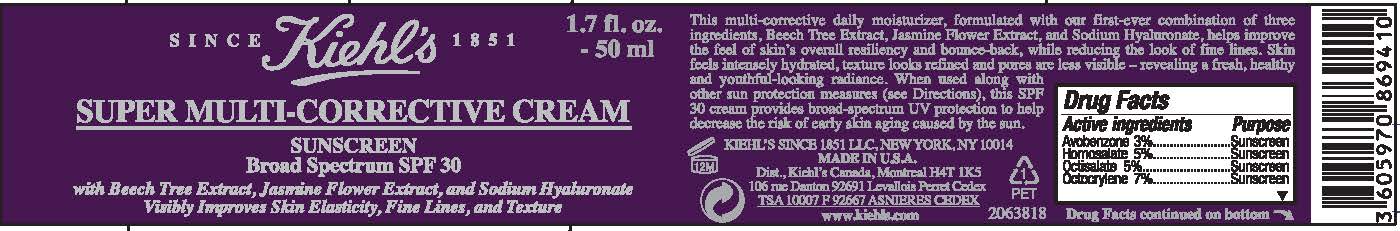 DRUG LABEL: Kiehls Since 1851 Super Multi Corrective Broad Spectrum SPF 30 Sunscreen
NDC: 49967-410 | Form: CREAM
Manufacturer: L’Oreal USA Products Inc
Category: otc | Type: HUMAN OTC DRUG LABEL
Date: 20240101

ACTIVE INGREDIENTS: AVOBENZONE 30 mg/1 mL; HOMOSALATE 50 mg/1 mL; OCTISALATE 50 mg/1 mL; OCTOCRYLENE 70 mg/1 mL
INACTIVE INGREDIENTS: WATER; GLYCERIN; DIMETHICONE; GLYCERYL MONOSTEARATE; HYDROXYPROPYL TETRAHYDROPYRANTRIOL; SILICON DIOXIDE; PEG-100 STEARATE; PROPYLENE GLYCOL; CANDELILLA WAX; PHENOXYETHANOL; STEARIC ACID; DICAPRYLYL CARBONATE; CETYL ALCOHOL; PALMITIC ACID; CAPRYLOYL SALICYLIC ACID; CAPRYLYL GLYCOL; XANTHAN GUM; DIMETHICONE/VINYL DIMETHICONE CROSSPOLYMER (SOFT PARTICLE); EDETATE DISODIUM ANHYDROUS; TOCOPHEROL; HYALURONATE SODIUM; ADENOSINE; LINALOOL, (+/-)-; SODIUM HYDROXIDE; JASMINUM OFFICINALE FLOWER; .BETA.-CITRONELLOL, (+/-)-; GERANIOL; CITRAL; BENZYL ALCOHOL; CITRIC ACID MONOHYDRATE

Drug Facts

Active ingredient

Avobenzone 3%

Homosalate 5%

Octisalate 5%

Octocrylene 7%

Purpose

Sunscreen

Uses

- helps prevent sunburn
- if used as directed with other sun protection measures (see Directions), decreases the risk of skin cancer and early skin aging caused by the sun

Warnings

For external use only

Do not use

on damaged or broken skin

When using this product

keep out of eyes. Rinse with water to remove.

Stop use and ask a doctor if

rash occurs

Keep out of reach of children.

If swallowed, get medical help or contact a Poison Control Center right away.

Directions

For sunscreen use:

- apply liberally 15 minutes before sun exposure
- reapply at least every 2 hours
- use a water resistant sunscreen if swimming or sweating
- Sun Protection Measures. Spending time in the sun increases your risk of skin cancer and early skin aging. To decrease this risk, regularly use a sunscreen with a Broad Spectrum SPF value of 15 or higher and other sun protection measures including:

● limit time in the sun, especially from 10 a.m. – 2 p.m.

● wear long-sleeved shirts, pants, hats, and sunglasses

- children under 6 months of age: Ask a doctor

Other information

protect the product in this container from excessive heat and direct sun

Inactive ingredients

water, glycerin, dimethicone, glyceryl stearate, hydroxypropyl tetrahydropyrantriol, silica, PEG-100 stearate, propylene glycol, euphorbia cerifera (candelilla) wax, phenoxyethanol, ammonium polyacryloyldimethyl taurate, stearic acid, dicaprylyl carbonate, cetyl alcohol, palmitic acid, capryloyl salicylic acid, caprylyl glycol, xanthan gum, dimethicone/vinyl dimethicone crosspolymer, fragrance, disodium EDTA, tocopherol, sodium hyaluronate, adenosine, linalool, sodium hydroxide, jasminum officinale (jasmine) flower extract, citronellol, geraniol, citral, benzyl alcohol, citric acid

Questions or comments?

Call toll free 1-800-946-4453

Monday - Friday (9 a.m. to 5 p.m. EST)